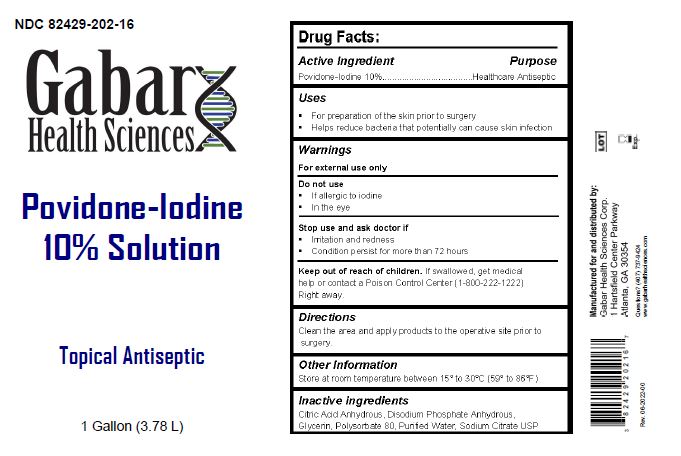 DRUG LABEL: Povidone-Iodine 10% Solution
NDC: 82429-202 | Form: LIQUID
Manufacturer: Gabar Health Sciences Corp.
Category: otc | Type: HUMAN OTC DRUG LABEL
Date: 20231021

ACTIVE INGREDIENTS: POVIDONE-IODINE 10 mg/1 mL
INACTIVE INGREDIENTS: ANHYDROUS CITRIC ACID; SODIUM PHOSPHATE DIBASIC DIHYDRATE; GLYCERIN; POLYSORBATE 80; WATER; SODIUM CITRATE

Povidone - Iodine 10%

ACTIVE INGREDIENT

POVIDONE IODINE 10%

Warnings

For external use only

Do Not Use

- if allergic to iodine
- in the eyes

Stop use and ask a doctor if

- irritation and redness develop
- condition persists for more than 72 hours

Keep out of reach of children. If swallowed, get medical help, or contact a Posion Control Center (1-800-222-1222) right away.

Inactive Ingredients

Povidone-iodine 10%

Purpose

Healthcare Antiseptic

Use

For preparation of the skin prior to surgery. Helps reduce bacteria that potentially can cause skin infection

Use

For preparation of the skin prior to surgery. Helps reduce bacteria that potentially can cause skin infection.

Directions

Clean the area. Apply product to the operative site prior to surgery.

Other

Store at controlled room temperature 15º-30ºC (59º-86ºF).

Questions?

1-470-737-9424

Principal Display Panel

NDC 82429-202-16

Gabar Health Sciences

Povidone-Iodine

10% Solution

Topical Antiseptic

1 Gallon (3.78 L)